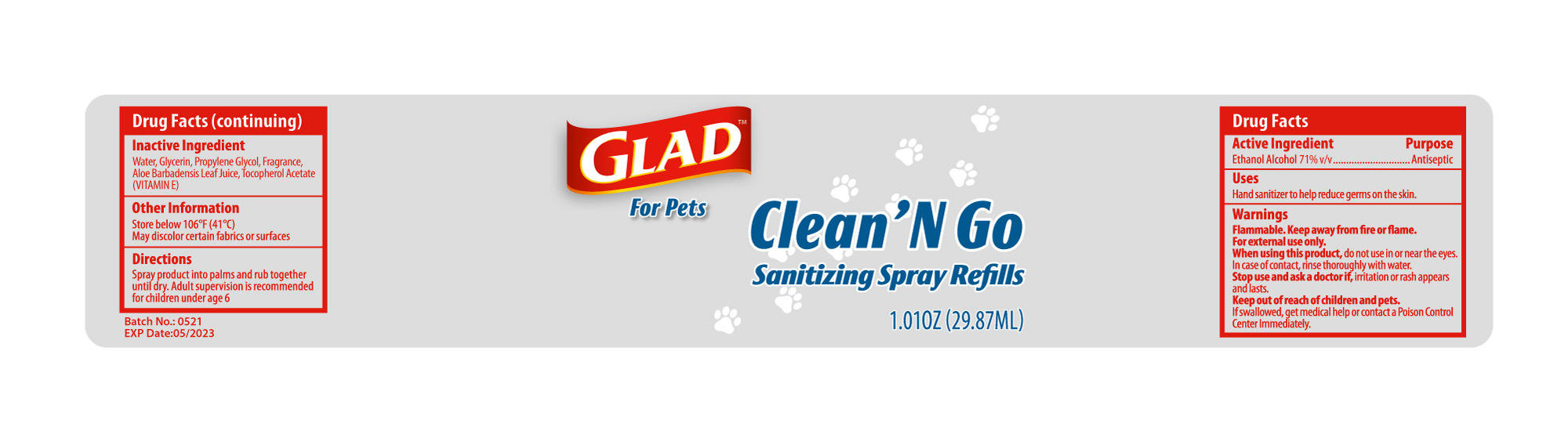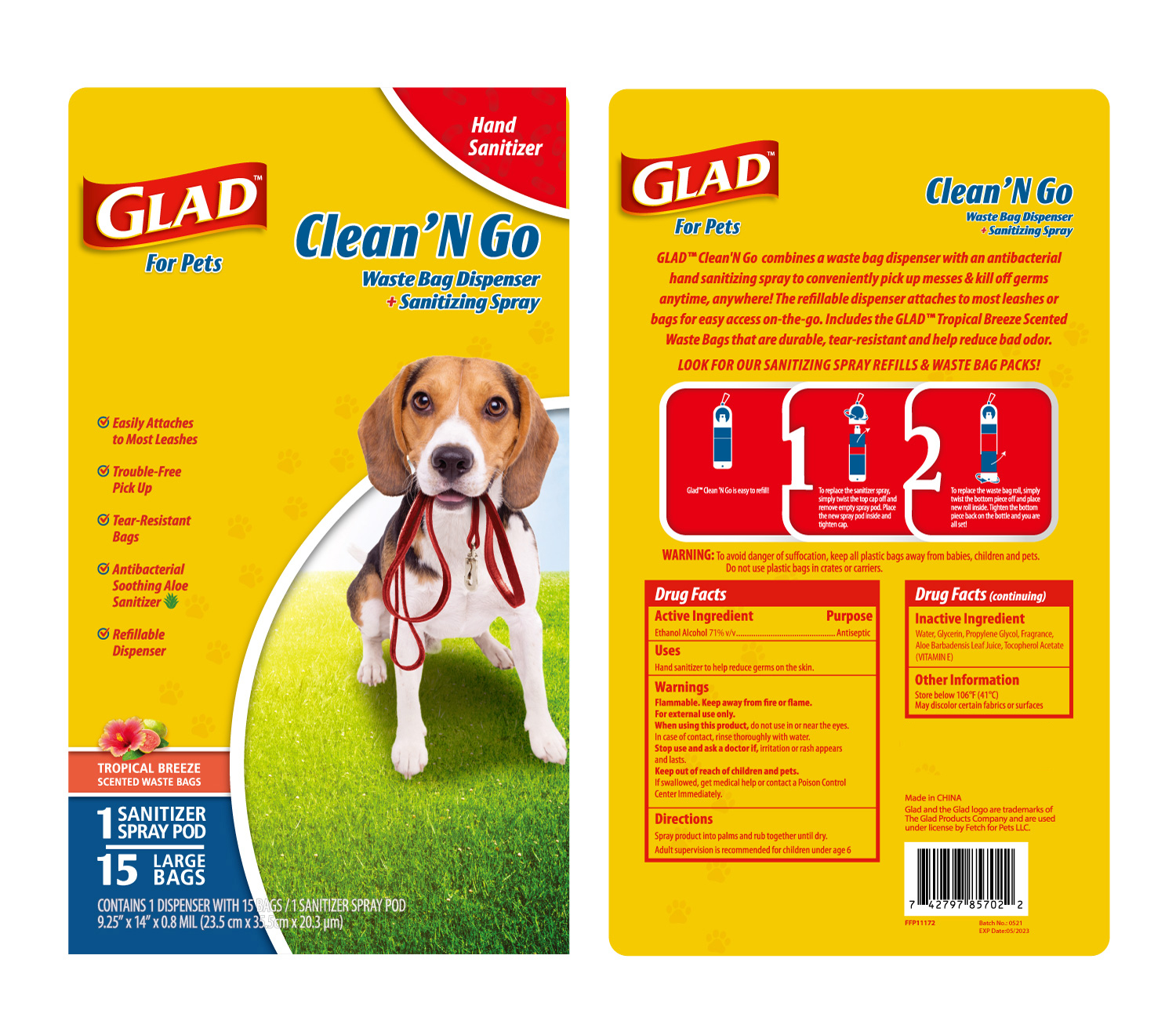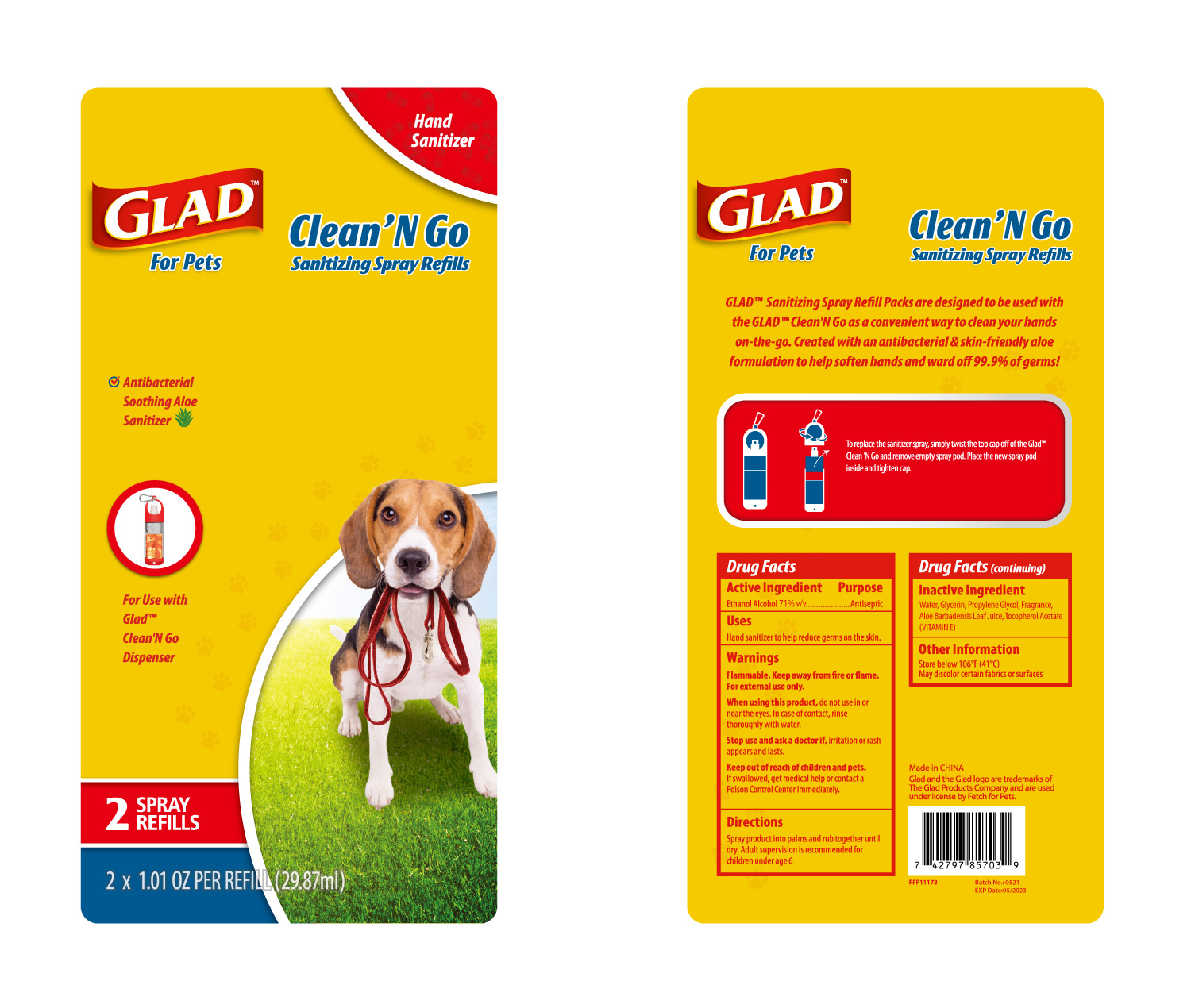 DRUG LABEL: HAND SANITIZER
NDC: 47993-328 | Form: LIQUID
Manufacturer: NINGBO JIANGBEI OCEAN STAR TRADING CO.,LTD
Category: otc | Type: HUMAN OTC DRUG LABEL
Date: 20210617

ACTIVE INGREDIENTS: ALCOHOL 71 mL/100 mL
INACTIVE INGREDIENTS: WATER; GLYCERIN; PROPYLENE GLYCOL; ALOE VERA LEAF; .ALPHA.-TOCOPHEROL ACETATE

47993-328

Active ingredients

Ethanol Alcohol 71% v/v

PURPOSE

Antiseptic

Uses：

Hand sanitizer to help reduce germs on the skin.

Warnings:

Flammable. Keep away from fire or flame.

For external use only.

When using this product, do not use in or near the eyes, In case of contact, rinse thoroughly with water.

Stop use and ask a doctor if, irritation or rash appears and lasts.

Keep out of reach of children and pets.

If swallowed, get medical help or contact a Poison Control Center Immediately.

Inactive ingredients:

Water, Glycerin, Propylene Glycol, Fragrance, Aloe Barbedensis Leaf Juice, Tocopherol Acetate (VITAMIN E)

Other information:

Store below 106℉(41℃).

May discolor certain fabrics.

Directions:

Spray product into palms and rub together until dry. Adult supervision is recommended for children under age 6.